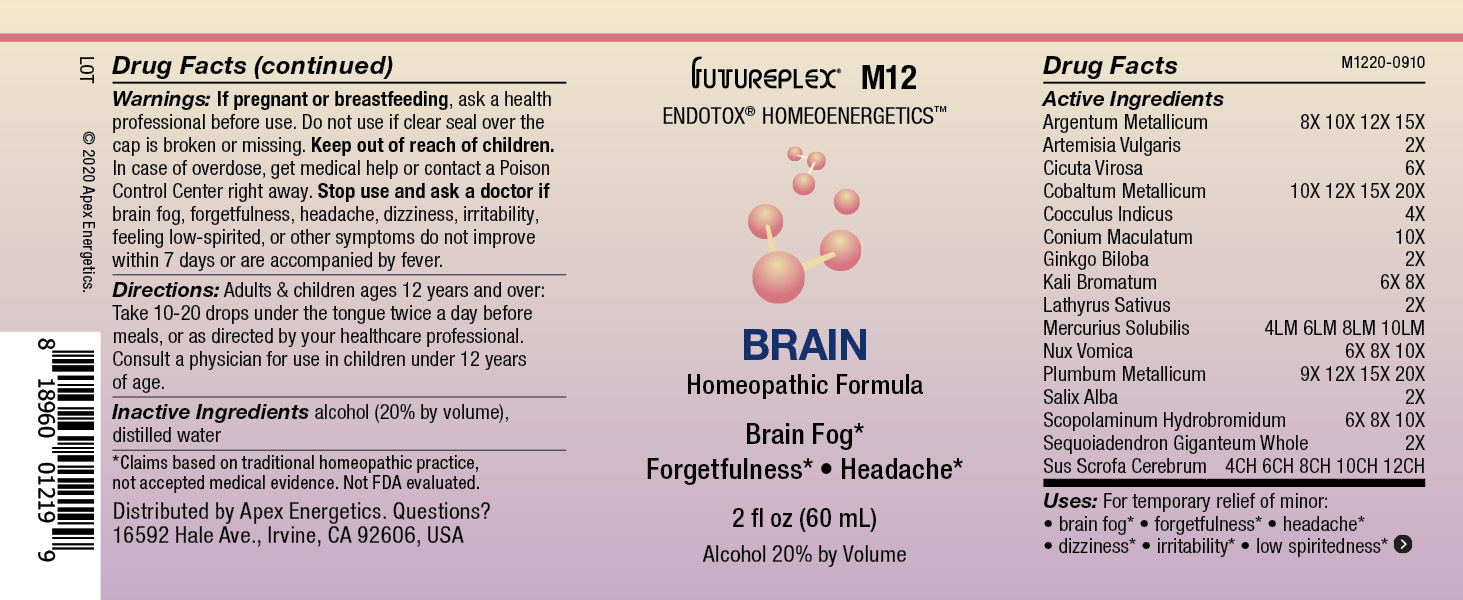 DRUG LABEL: M12
NDC: 63479-1312 | Form: SOLUTION/ DROPS
Manufacturer: Apex Energetics Inc
Category: homeopathic | Type: HUMAN OTC DRUG LABEL
Date: 20240108

ACTIVE INGREDIENTS: SEQUOIADENDRON GIGANTEUM WHOLE 2 [hp_X]/1 mL; MERCURIUS SOLUBILIS 10 [hp_Q]/1 mL; LEAD 20 [hp_X]/1 mL; SALIX ALBA BARK 2 [hp_X]/1 mL; SCOPOLAMINE HYDROBROMIDE 10 [hp_X]/1 mL; SUS SCROFA CEREBRUM 12 [hp_C]/1 mL; CICUTA VIROSA ROOT 6 [hp_X]/1 mL; SILVER 15 [hp_X]/1 mL; COBALT 20 [hp_X]/1 mL; GINKGO 2 [hp_X]/1 mL; ARTEMISIA VULGARIS ROOT 2 [hp_X]/1 mL; STRYCHNOS NUX-VOMICA SEED 10 [hp_X]/1 mL; ANAMIRTA COCCULUS SEED 4 [hp_X]/1 mL; CONIUM MACULATUM FLOWERING TOP 10 [hp_X]/1 mL; POTASSIUM BROMIDE 8 [hp_X]/1 mL; LATHYRUS SATIVAS SEED 2 [hp_X]/1 mL
INACTIVE INGREDIENTS: ALCOHOL; WATER

M12

Active Ingredients
Argentum Metallicum | 8X 10X 12X 15X
Artemisia Vulgaris | 2X
Cicuta Virosa | 6X
Cobaltum Metallicum | 10X 12X 15X 20X
Cocculus Indicus | 4X
Conium Maculatum | 10X
Ginkgo Biloba | 2X
Kali Bromatum | 6X 8X
Lathyrus Sativus | 2X
Mercurius Solubilis | 4LM 6LM 8LM 10LM
Nux Vomica | 6X 8X 10X
Plumbum Metallicum | 9X 12X 15X 20X
Salix Alba | 2X
Scopolaminum Hydrobromidum | 6X 8X 10X
Sequoiadendron Giganteum Whole | 2X
Sus Scrofa Cerebrum | 4CH 6CH 8CH 10CH 12CH

INDICATIONS AND USAGE

Uses:

For temporary relief of minor:

brain fog*

forgetfulness*

headache*

dizziness*

irritability*

low spiritedness*

*Claims based on traditional homeopathic practice, not accepted medical evidence. Not FDA evaluated.

Warnings:

PREGNANCY OR BREAST FEEDING

If pregnant or breastfeeding, ask a health professional before use.

Do not use if clear seal over the cap is broken or missing.

Keep out of reach of children. In case of overdose, get medical help or contact a Poison Control Center right away.

Stop use and ask a doctor if brain fog, forgetfulness, headache, dizziness, irritability, feeling low-spirited, or other symptoms do not improve within 7 days or are accompanied by fever.

Directions:

Adults & children ages 12 years and over: Take 10-20 drops under the tongue twice a day before meals, or as directed by your healthcare professional. Consult a physician for use in children under 12 years of age.

Inactive Ingredients

alcohol (20% by volume), distilled water

Distributed by Apex Energetics. Questions?

16592 Hale Ave., Irvine, CA 92606, USA

PACKAGE LABEL

FUTUREPLEX® M12

ENDOTOX® HOMEOENERGETICS™

BRAIN

Homeopathic Formula

Brain Fog*

Forgetfulness*

Headache*

2 fl oz (60 mL)

Alcohol 20% by Volume